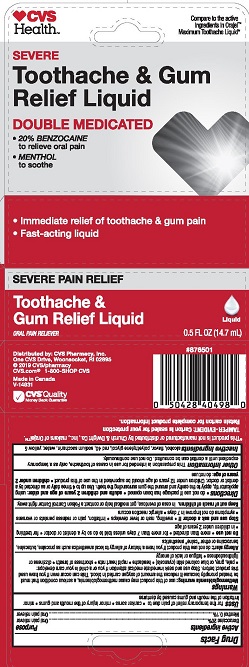 DRUG LABEL: CVS 2x Liq (CSR)
NDC: 49354-353 | Form: LIQUID
Manufacturer: CSR Cosmetic Solutions
Category: otc | Type: HUMAN OTC DRUG LABEL
Date: 20210902

ACTIVE INGREDIENTS: MENTHOL, UNSPECIFIED FORM 0.1 mg/100 mL; BENZOCAINE 20 mg/100 mL
INACTIVE INGREDIENTS: POLYETHYLENE GLYCOL 400; ALCOHOL; SACCHARIN SODIUM; FD&C YELLOW NO. 5; FD&C RED NO. 40; WATER

5820353 CVS 2x Liq (CSR)

ACTIVE INGREDIENT

Benzocaine

Menthol

PURPOSE

Oral pain reliever

Oral pain reliever

INDICATIONS AND USAGE

fo rthe temporary relief of pain due to: * canker sores * minor injury of the mouth and gums * minor irritation of the mouth and gums caused by dentures

WARNINGS

Methemoglobinemia warning: use of this product may cause methemoglobinemia, a serious condition that must be treated promptly because it reduces the amount of oxygen carried in blood. This can occur even if you have used this product before. Stop use and seek immediate medical attention if you or a child in your care develops: * pale, gray, or blue colored skin (cyanosis) * headache * rapid heart rate * shortness of breath * dizziness or lightheadedness * fatigue or lack of energy

Allergy alert: do not use this product if you have a history of allergy to local anesthetics such as procaine, butacaine, benzocaine, or other "caine" anesthetics

Do not use * more than directed * for more than 7 days unless told to do so by a dentist or doctor * for teething * in children under 2 years of age

Stop use and ask a doctor if * swelling, rash or fever develops * irritation, pain or redness persists or worsens * symptoms do not improve in 7 days * allergic reaction occurs

Keep out of reach of children. In case of overdose, get medical help or contact a Poison Control Center right away.

do not use if package has been opened * adults and children 2 years of age and older: using applicator tip, apply to the cavity and around the gum surrounding the tooth. Use up to 4 times daily or as directed by a dentist or doctor. Children under 12 years of age should be supervised in the use of this product * children under 2 years of age: do not use

OTHER SAFETY INFORMATION

this preparation is intended for use in cases of toothache, only as a temporary expedient until a dentist can be consulted. Do not use continually.

INACTIVE INGREDIENT

alcohol, flavor, polyethylene glycol, red 40, sodium saccharin, water, yellow 5